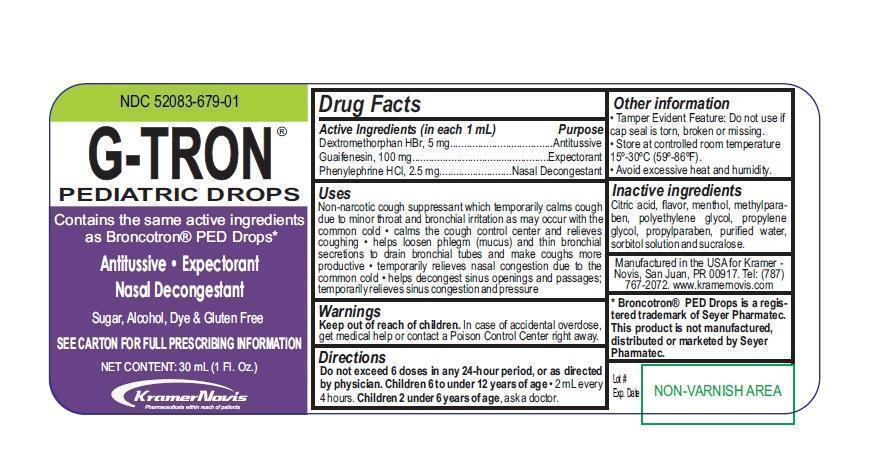 DRUG LABEL: G-TRON PEDIATRIC DROPS
NDC: 52083-679 | Form: SOLUTION/ DROPS
Manufacturer: KRAMER NOVIS
Category: otc | Type: HUMAN OTC DRUG LABEL
Date: 20191113

ACTIVE INGREDIENTS: DEXTROMETHORPHAN HYDROBROMIDE 5 mg/1 mL; GUAIFENESIN 100 mg/1 mL; PHENYLEPHRINE HYDROCHLORIDE 2.5 mg/1 mL
INACTIVE INGREDIENTS: CITRIC ACID MONOHYDRATE; MENTHOL; METHYLPARABEN; POLYETHYLENE GLYCOL 1000; PROPYLENE GLYCOL; PROPYLPARABEN SODIUM; WATER; SORBITOL; SUCRALOSE

G-TRON PEDIATRIC DROPS

Active Ingredients

Dextromethorphan HBr,5 mg
Guaifenesin, 100 mg
Phenylephrine HCL 2.5 mg

Purpose

Antitussive

Expectorant

Nasal Decongestant

Keep out of reach of children. In case of accidental overdose, get medical help or contact a Poison Control Center right away.

Uses

Non-narcotic cough suppressant which temporarily calms cough due to minor throat and bronchial irritation as may occur with the common cold • calms the cough control center and relieves coughing • helps loosen phlegm (mucus) and thin bronchial secretions to drain bronchial tubes and make coughs more productive • temporarily relieves nasal congestion due to the common cold • helps decongest sinus openings and passages; temporarily relieves sinus congestion and pressure

Warnings

Tamper Evident Feature: Do not use if cap seal is torn, broken or missing.

Directions

Do not exceed 6 doses in any 24-hour period, or as directed by physician. Children 6 to under 12 years of age • 2 mL every 4 hours. Children 2 to under 6 years of age, ask a doctor.

Other information

- Tamper Evident Feature: Do not use if cap seal is torn, broken or missing.
- Store at controlled room temperature 15º-30ºC (59º-86ºF).
- Avoid excessive heat and humidity.

INACTIVE INGREDIENT

Citric acid, flavor, menthol, methylparaben, polyethylene glycol, propylene glycol, propylparaben, purified water, sorbitol solution and sucralose.

Manufactured in the USA for Kramer -Novis, San Juan, PR 00917.

Tel: (787)767-2072. www.kramernovis.com

* Broncotron® PED Drops is a registered trademark of Seyer Pharmatec.
This product is not manufactured, distributed or marketed by Seyer Pharmatec.